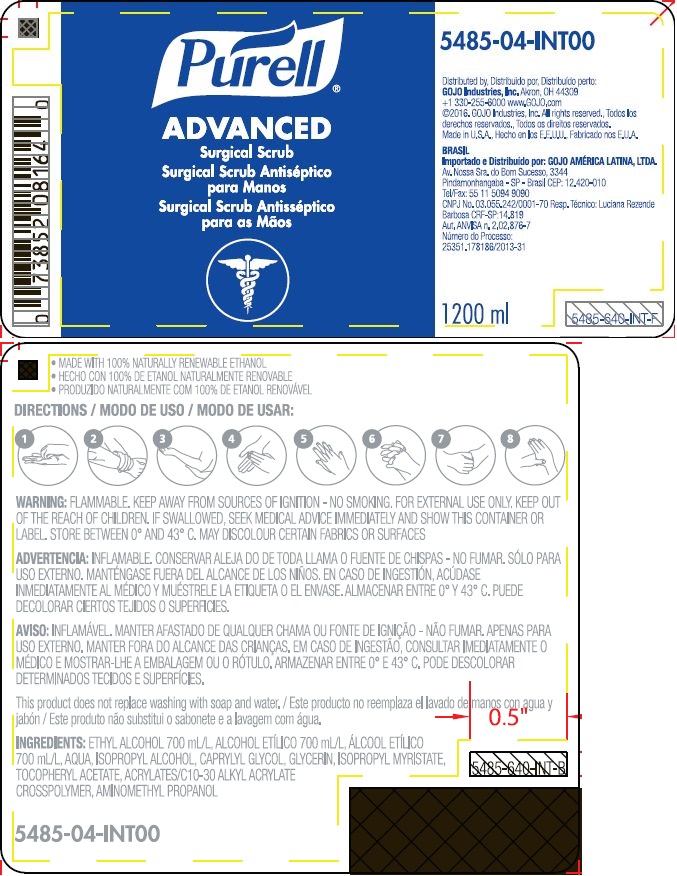 DRUG LABEL: PURELL Advanced for Surgical Scrub Use
NDC: 21749-031 | Form: GEL
Manufacturer: GOJO Industries, Inc.
Category: otc | Type: HUMAN OTC DRUG LABEL
Date: 20241231

ACTIVE INGREDIENTS: ALCOHOL 0.7 mL/1 mL
INACTIVE INGREDIENTS: WATER; ISOPROPYL ALCOHOL; CAPRYLYL GLYCOL; GLYCERIN; ISOPROPYL MYRISTATE; .ALPHA.-TOCOPHEROL ACETATE; CARBOMER INTERPOLYMER TYPE A (ALLYL SUCROSE CROSSLINKED); AMINOMETHYLPROPANOL

PURELL Advanced for Surgical Scrub Use